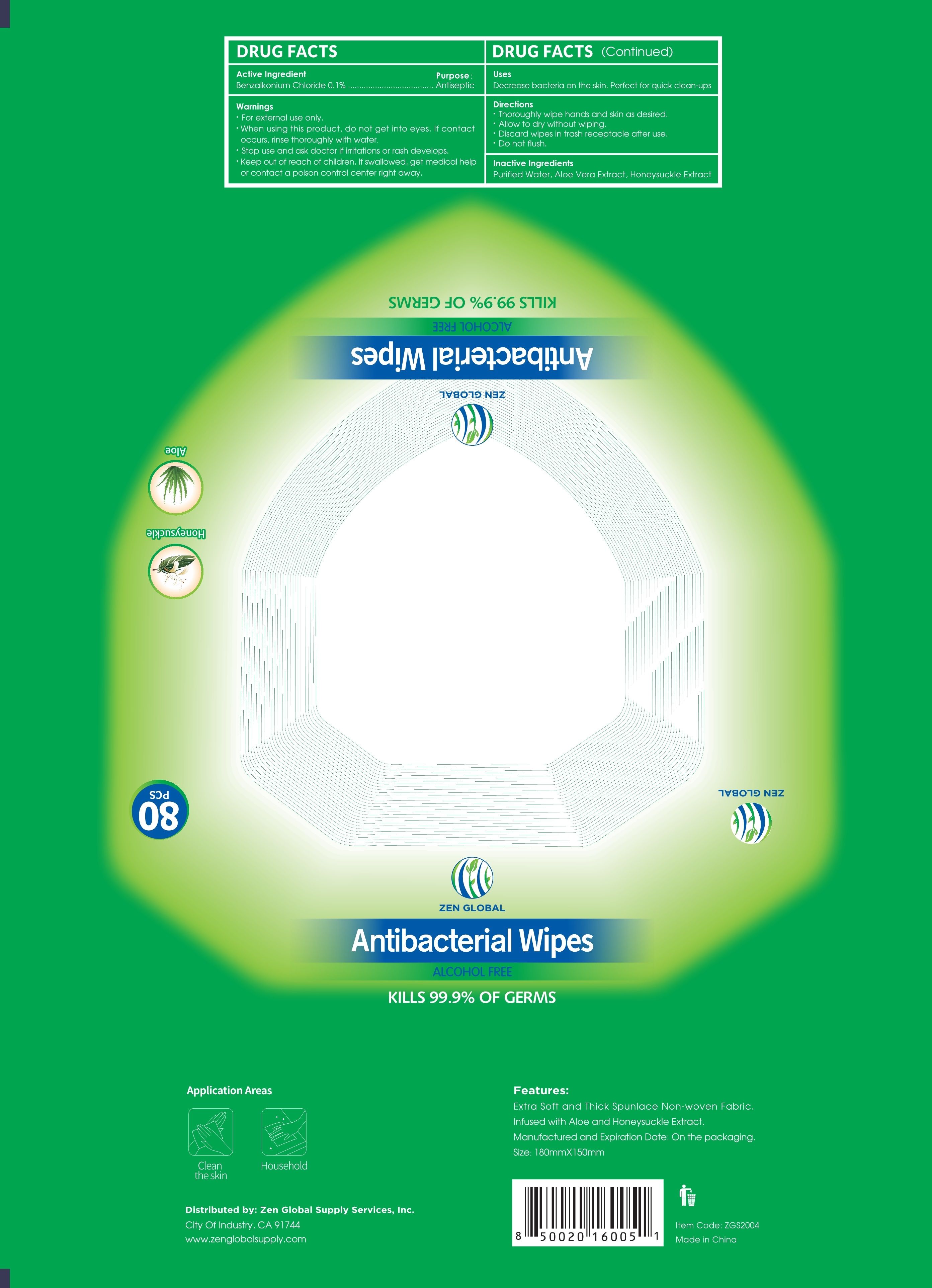 DRUG LABEL: Antibacterial wipes
NDC: 42129-011 | Form: CLOTH
Manufacturer: Fustin(Xiamen) Commodity Co., ltd
Category: otc | Type: HUMAN OTC DRUG LABEL
Date: 20200716

ACTIVE INGREDIENTS: BENZALKONIUM CHLORIDE 0.1 1/100 1
INACTIVE INGREDIENTS: ALOE VERA LEAF; LONICERA DASYSTYLA WHOLE; WATER

Antibacterial wipes

Active Ingredient(s)

Benzalkonium Chloride 0.1%

Purpose

/

Use

Decrease bacteria on the skin. Perfect for quick clean-ups

Warnings

For external use only.

Keep out of reach of children. If swallowed, get medical help or contact a Poison Control Center right away

When using this product, do not get into eyes. If contact occurs, rinse thoroughly with water.

Do not use

/

Stop use and ask doctor if irritations or rash develops.

Directions

Thoroughly wipe hands and skin as desired
Allow to dry without wiping
Discard wipes in trash receptacle after use
Do not flush

Inactive ingredients

Purified Water, Aloe Vera Extract, Honeysuckle Extract